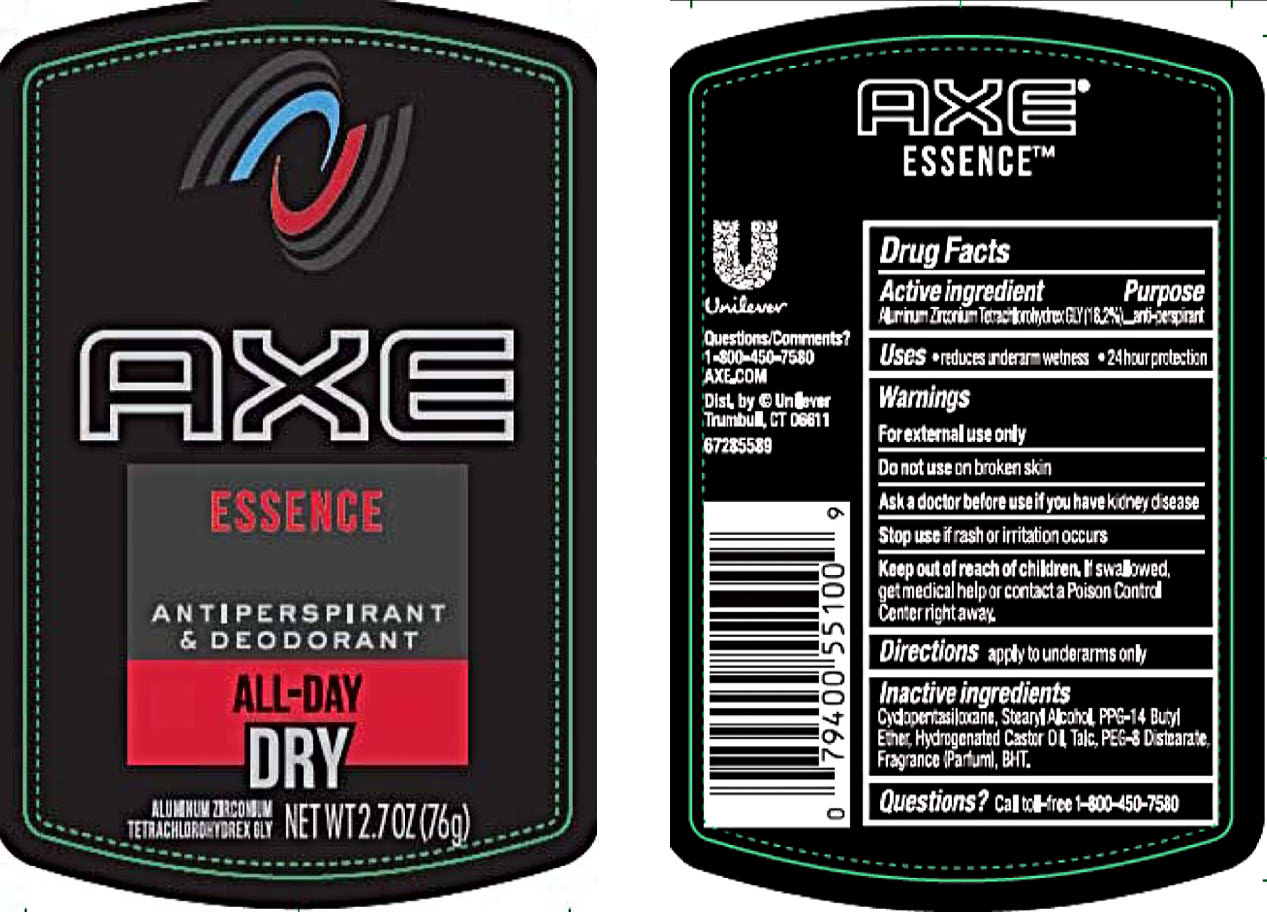 DRUG LABEL: Axe
NDC: 64942-1538 | Form: STICK
Manufacturer: Conopco Inc. d/b/a/ Unilever
Category: otc | Type: HUMAN OTC DRUG LABEL
Date: 20211201

ACTIVE INGREDIENTS: ALUMINUM ZIRCONIUM TETRACHLOROHYDREX GLY 18.2 g/100 g
INACTIVE INGREDIENTS: PEG-8 DISTEARATE; TALC; CYCLOMETHICONE 5; HYDROGENATED CASTOR OIL; BUTYLATED HYDROXYTOLUENE; PPG-14 BUTYL ETHER; STEARYL ALCOHOL

Axe Essence Antiperspirant and Deodorant

AXE ESSENCE ANTIPERSPIRANT AND DEODORANT - aluminum zirconium tetrachlorohydrex gly stick

Axe Essence Antiperspirant and Deodorant

Drug Facts

Active ingredient

Aluminum Zirconium Tetrachlorohydrex GLY (18.2 %)

Purpose

antiperspirant

Uses

• reduces underarm wetness

• 24 Hour Protection

Warnings

• For external use only.
• Do not use on broken skin .
• Ask a doctor before use if you have kidney disease.
• Stop use if rash or irritation occurs.

• Keep out of reach of children.

If swallowed, get medical help or contact a Poison Control Center right away.

Directions

apply to underarms only

Inactive ingredients

Cyclopentasiloxane, Stearyl Alcohol, PPG-14 Butyl Ether, Hydrogenated Castor Oil, Talc, PEG-8 Distearate, Fragrance (Parfum), BHT.

Questions?

Call toll-free 1-800-450-7580